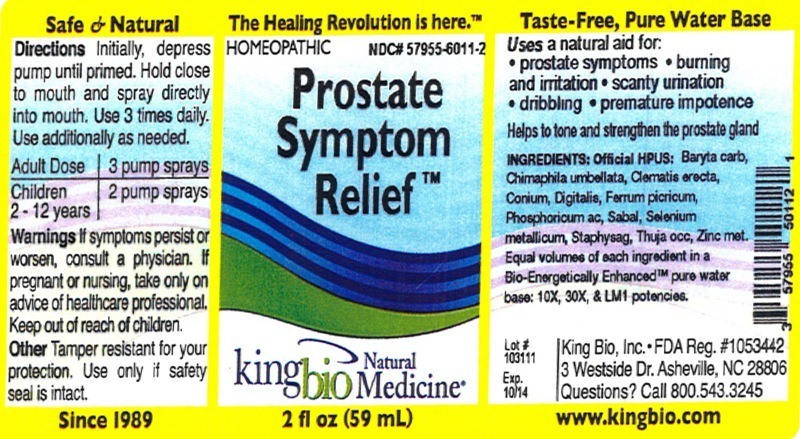 DRUG LABEL: Prostate Symptom Relief
NDC: 57955-6011 | Form: LIQUID
Manufacturer: King Bio Inc.
Category: homeopathic | Type: HUMAN OTC DRUG LABEL
Date: 20120619

ACTIVE INGREDIENTS: BARIUM CARBONATE 10 [hp_X]/59 mL; CHIMAPHILA UMBELLATA 10 [hp_X]/59 mL; CLEMATIS RECTA FLOWERING TOP 10 [hp_X]/59 mL; CONIUM MACULATUM FLOWERING TOP 10 [hp_X]/59 mL; DIGITALIS 10 [hp_X]/59 mL; FERRIC PICRATE 10 [hp_X]/59 mL; PHOSPHORIC ACID 10 [hp_X]/59 mL; SAW PALMETTO 10 [hp_X]/59 mL; SELENIUM 10 [hp_X]/59 mL; DELPHINIUM STAPHISAGRIA SEED 10 [hp_X]/59 mL; THUJA OCCIDENTALIS LEAFY TWIG 10 [hp_X]/59 mL; ZINC 10 [hp_X]/59 mL
INACTIVE INGREDIENTS: WATER

Prostate Symptom Relief

Active Ingredients

Official HPUS

Baryta carbonica, Chimaphila umbellata, Clematis erecta, Conium maculatum, Digitalis purpurea, Ferrum picricum, Phosphoricum acidum, Sabal serrulata, Selenium metallicum, Staphysagria, Thuja occidentalis, Zincum metallicum.

Reference image prostate.jpg

Inactive Ingredient

Equal volumes of each ingredient in a Bio-Energetically Enhanced pure water base: 10X, 30X, and LM1 potencies.

Reference image prostate.jpg

Purpose

Uses a natural aid for:

- prostate symptoms
- burning and irritation
- scanty urination
- dribbling
- premature impotence

Helps to tone and strengthen the prostate gland.

Reference image prostate.jpg

Warnings

If symptoms persist or worsen, consult a physician. If pregnant or nursing, take only on advice of healthcare professional. Keep out of reach of children.

Other: Tamper resistant for your protection. Use only if safety seal is intact.

Reference image prostate.jpg

Keep out of reach of children.

Reference image prostate.jpg

Indications and Usage

Uses a natural aid for: prostate symptoms, burning and irritation, scanty urination, dribbling, premature impotence.

Helps to tone and strengthen the prostate gland.

Reference image prostate.jpg

Dosage and Administration

Directions: Initially, depress pump until primed. Hold close to mouth and spray directly into mouth. Use 3 times daily. Use additionally as needed.

Adult Dose 3 pump sprays

Children 2-12 years 2 pump sprays

Reference image prostate.jpg

PACKAGE LABEL

King Bio Inc.

3 Westside Drive

Asheville, NC 28806

Questions? Call 800.543.3245

www.kingbio.com

Reference image prostate.jpg